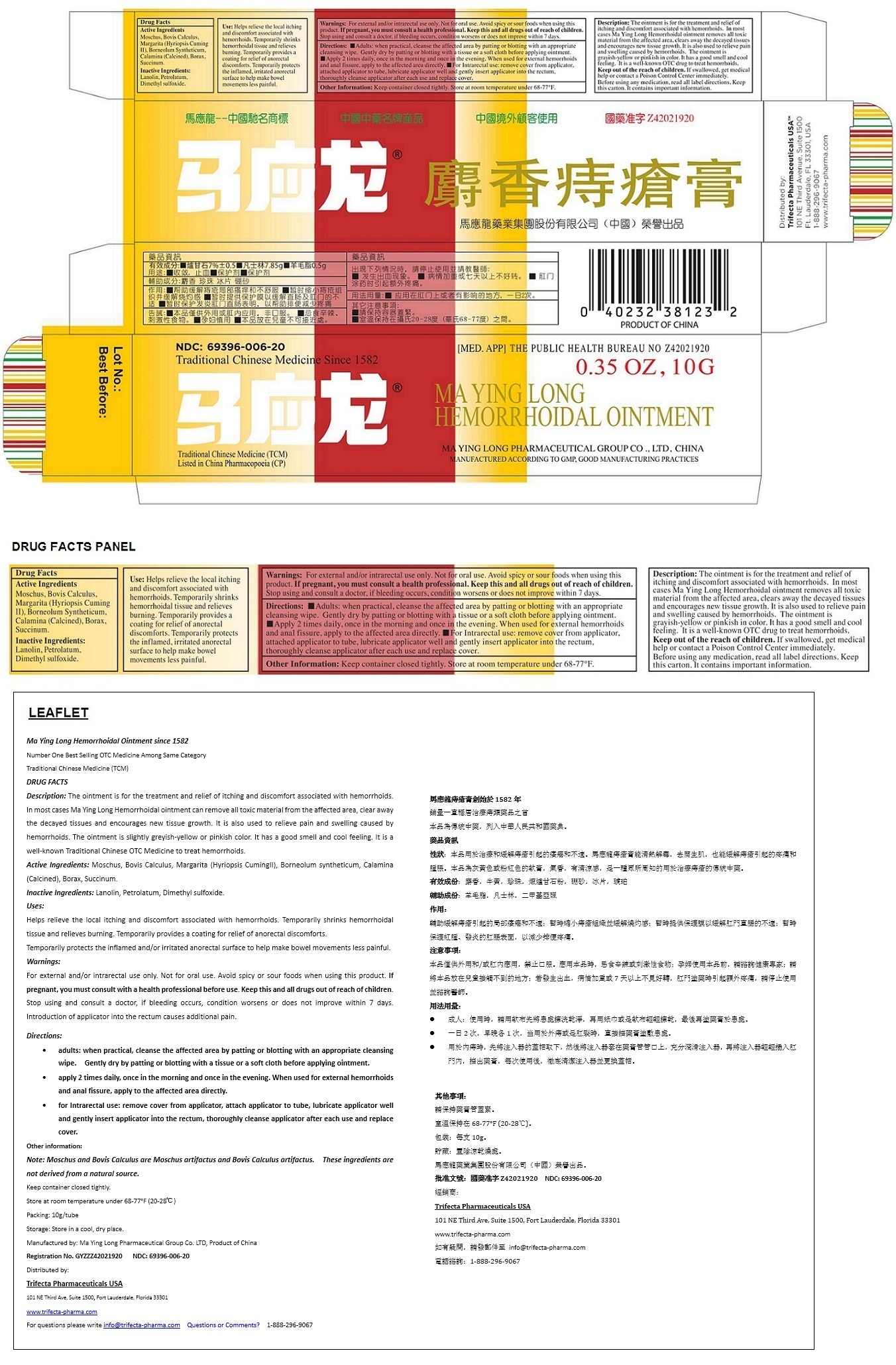 DRUG LABEL: MA YING LONG HEMORRHOIDAL
NDC: 69396-006 | Form: OINTMENT
Manufacturer: Trifecta Pharmaceuticals Usa Llc
Category: otc | Type: HUMAN OTC DRUG LABEL
Date: 20160223

ACTIVE INGREDIENTS: MOSCHUS BEREZOVSKII MUSK SAC RESIN 0.15 g/10 g; BOS TAURUS GALLSTONE 0.1 g/10 g; PEARL (HYRIOPSIS CUMINGII) 0.25 g/10 g; BORNEOL 0.2 g/10 g; AMBER 0.1 g/10 g; ZINC CARBONATE 0.65 g/10 g; SODIUM BORATE 0.2 g/10 g
INACTIVE INGREDIENTS: LANOLIN; PETROLATUM; DIMETHYL SULFOXIDE

MA YING LONG HEMORRHOIDAL OINTMENT

Active Ingredients

Moschus

Bovis Calculus

Margarita (Hyriopsis Cuming II)

Borneolum syntheticum

Calamina (Calcined)

Borax

Succinum

Purpose

Formulated for symptoms associated with hemorrhoids such as itching, discomfort associated with hemorrhoids

KEEP OUT OF REACH OF CHILDREN

Keep out of the reach of children. If swallowed, get medical help or contact a Poison Control Center immediately.

INDICATIONS AND USAGE

Use: Helps relieve the local itching and discomfort associated with hemorrhoids. Temporarily shrinks hemorrhoidal tissue and relieves burning. Temporarily provides a coating for relief of anorectal discomforts. Temporarily protects the inflamed, irritated anorectal surface to help make bowel movements less painful.

WARNINGS

Warnings: For external and/or intrarectal use only. Not for oral use. Avoid spicy or sour foods when using this product. If pregnant, please consult a health professional. Keep this and all drugs out of reach of children. Stop using and consult a doctor, if bleeding occurs, condition worsens or does not improve within 7 days. Introduction of applicator into the rectum causes additional pain.

Directions:

• Adults: when practical, cleanse the affected area by patting or blotting with an appropriate cleansing wipe. Gently dry by patting or blotting with a tissue or a soft cloth before applying ointment. • Apply 2 times daily, once in the morning and once in the evening. When used for external hemorrhoids and anal fissure, apply to the affected area directly. • For Intrarectal use: remove cover from applicator, attached applicator to tube, lubricate applicator well and gently insert applicator into the rectum, thoroughly cleanse applicator after each use and replace cover.

Inactive Ingredients:

Lanolin, Petrolatum, Dimethyl sulfoxide.

Other Information: Keep container closed tightly. Store at room temperature under 68-77°F (20-28℃). Storage: Store in a cool, dry place.

Note: Moschus and Bovis Calculus are Moschus artifactus and Bovis artifactus. These ingredients are not derived from a natural source.

Packing: 10g/tube

For questions please write info@trifecta-pharma.com

Questions or Comments? 1-888-296-9067

Description: The ointment is for the treatment and relief of itching and discomfort associated with hemorrhoids. In most cases Ma Ying Long Hemorrhoidal ointment can clear heat and toxic material, remove the putrid tissues and promote their regeneration. It is also used to relieve pain and swelling caused by hemorrhoids. The ointment is grey-yellow or pink color, with fragrant smell and has a cool feeling. It is a well-known OTC drug to treat hemorrhoids.

Before using any medication, read all label directions. Keep this carton. It contains important information.

Traditional Chinese Medicine Since 1582

Traditional Chinese Medicine (TCM)
Listed in China Pharmacopoeia (CP)

Manufactured by: Ma Ying Long Pharmaceutical Group Co. LTD, Product of China

Registration No. GYZZZ42021920

Distributed by:

Trifecta Pharmaceuticals USA™

101 NE Third Avenue, Suite 1500
Ft. Lauderdale, FL 33301, USA
1-888-296-9067
www.trifecta-pharma.com